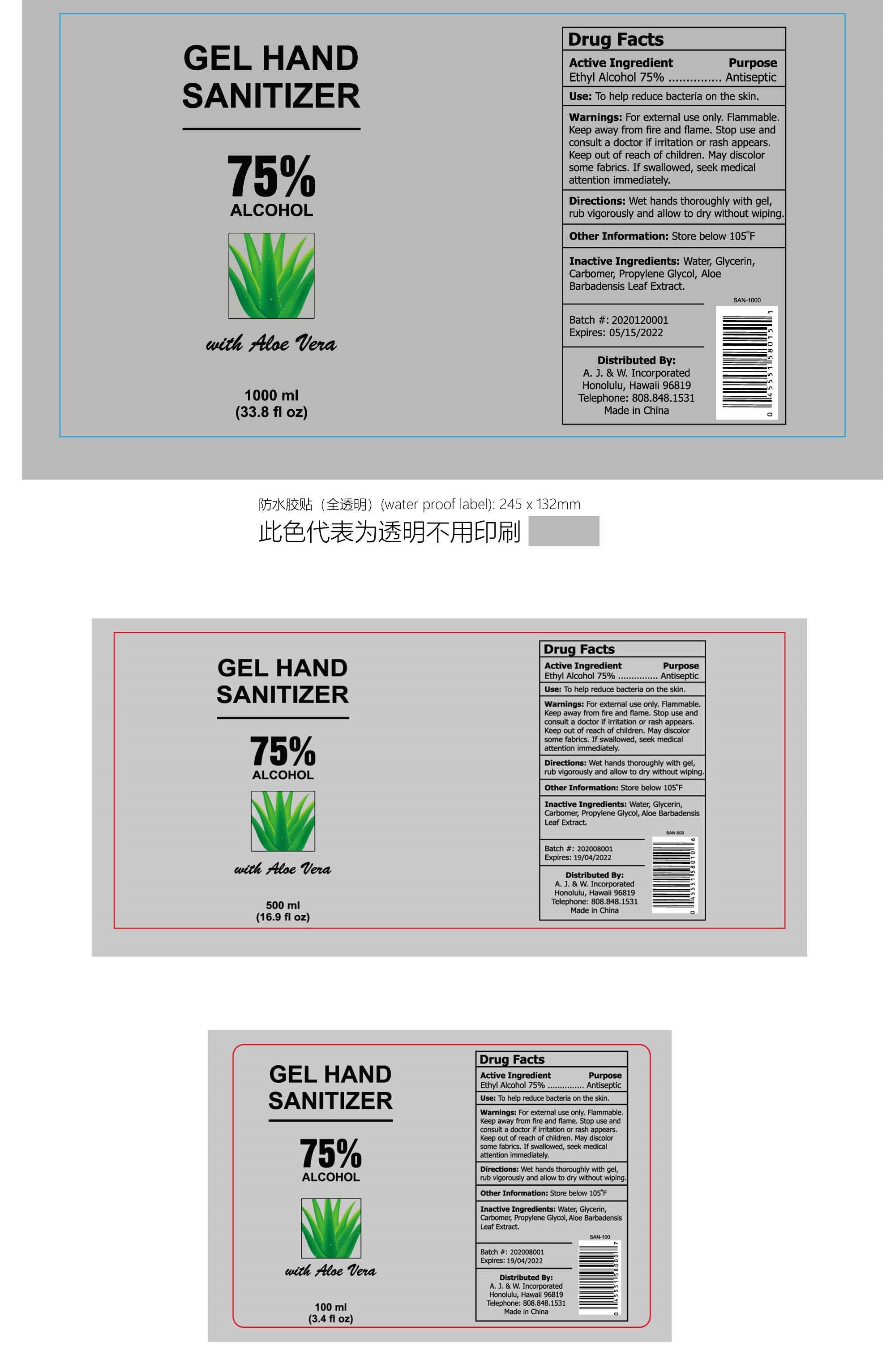 DRUG LABEL: Hand Sanitizer
NDC: 75742-010 | Form: GEL
Manufacturer: Zhejiang Guoyao Jingyue Aerosol Co., Ltd.
Category: otc | Type: HUMAN OTC DRUG LABEL
Date: 20200706

ACTIVE INGREDIENTS: ALCOHOL 75 mL/100 mL
INACTIVE INGREDIENTS: PROPYLENE GLYCOL; CARBOMER 940; WATER; GLYCERIN; ALOE VERA LEAF

GEL HAND SANITIZER WITH ALOE VERA

Active Ingredient

Ethyl Alcohol 75%

Purpose

Antiseptic

Uses

Hand Sanitizer to help reduce bacteria that potentially can cause disease. For use when soap and water are not available.

Warnings

For external use only. Flammable, keep away from fire and flame.

Stop use and consult a doctor if irritation or rash appears.

Keep out of reach of children.

DO NOT USE

If swallowed, seek medical attention immediately.

Directions

Wet hands thoroughly with gel, rub vigorously and allow to dry without wiping.

Other information

Store below 105°F. May discolor certain fabrics

INACTIVE INGREDIENT

Water, Glycerin, Carbomer, Propylene Glycol, Aloe Barbadensis Leaf Extract.

PACKAGE LABEL

1000ml, Package NDC: 75742-010-10; 500ml, Package NDC: 75742-010-05; 100ml, Package NDC: 75742-010-01